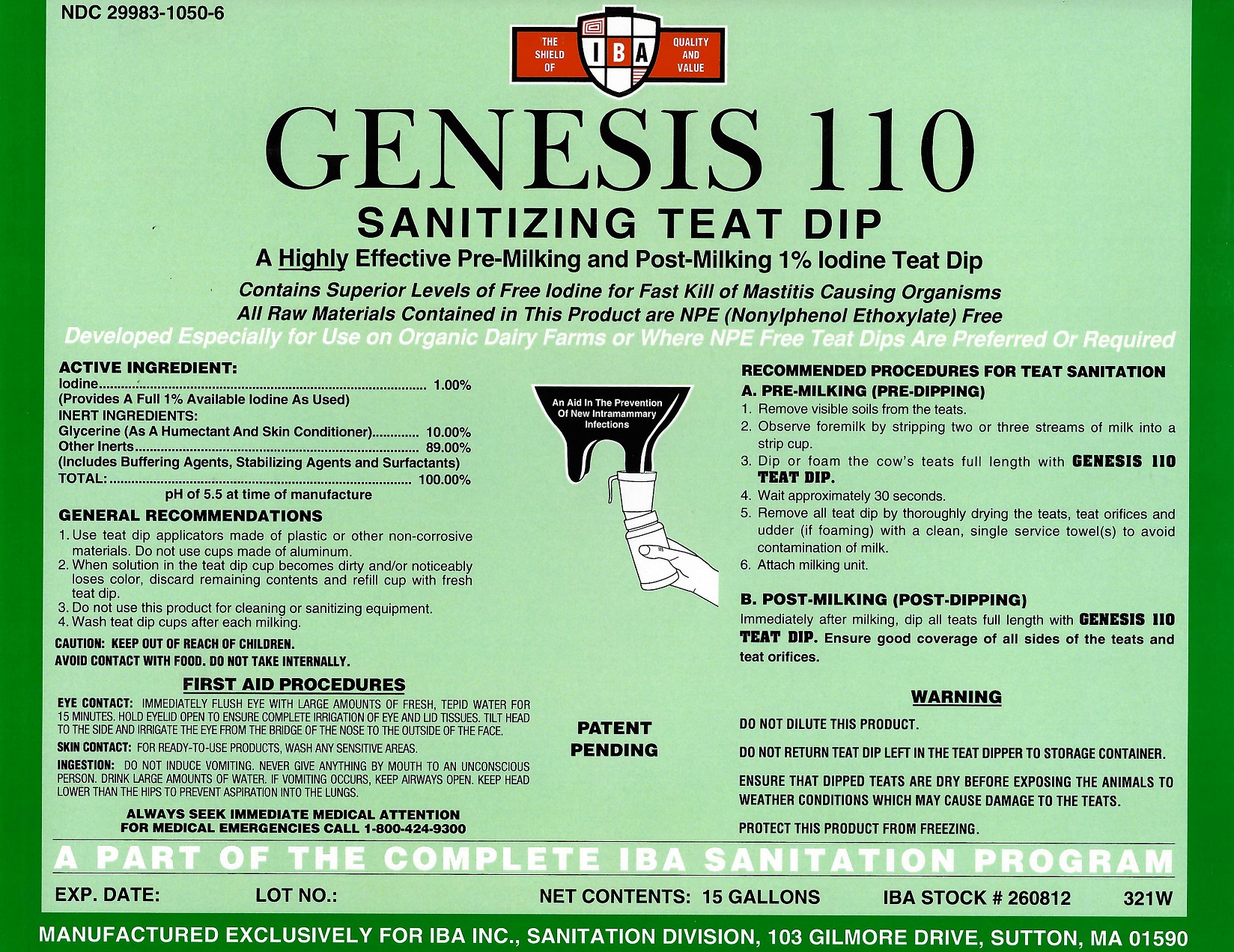 DRUG LABEL: Genesis 110
NDC: 29983-1050 | Form: LIQUID
Manufacturer: IBA
Category: animal | Type: OTC ANIMAL DRUG LABEL
Date: 20251126

ACTIVE INGREDIENTS: IODINE 1.0 kg/100 kg

Genesis 110

ACTIVE INGREDIENT

Iodine...........................................................1.00%

INERT INGREDIENTS

Glycerine.....................................................10.00%
Other Inerts.................................................89.00%

(Includes Buffering Agents, Stabilizing Agents and Surfactants)

TOTAL:......................................................100.00%

This product contains highly effective levels of

free iodine for fast kill of mastitis causing organisms.

WARNING

DO NOT DILUTE THIS PRODUCT.

DO NOT RETURN TEAT DIP LEFT IN THE TEAT DIPPER TO STORAGE CONTAINER.

ENSURE THAT DIPPED TEATS ARE DRY BEFORE EXPOSING THE ANIMALS TO WEATHER CONDITIONS WHICH MAY CAUSE DAMAGE TO THE TEATS.

PROTECT THIS PRODUCT FROM FREEZING.

NOT FOR HUMAN USE.

CAUTION: KEEP OUT OF REACH OF CHILDREN.

AVOID CONTACT WITH FOOD. DO NOT TAKE INTERNALLY.

FIRST AID PROCEDURES

EYECONTACT: IMMEDIATELY FLUSH EYE WITH LARGE AMOUNTS OF FRESH, TEPID WATER FOR 15 MINUTES. HOLD EYELID OPEN TO ENSURE COMPLETE IRRIGATION OF EYE AND LID TISSUES. TILT HEAD TO THE SIDE AND IRRIGATE THE EYE FROM THE BRIDGE OF THE NOSE TO THE OUTSIDE OF THE FACE.

SKIN CONTACT: FOR READY-TO-USE PRODUCTS, WASH ANY SENSITIVE AREAS.

INGESTION: DO NOT INDUCE VOMITING. NEVER GIVE ANYTHING BY MOUTH TO AN UNCONSCIOUS PERSON. DRINK LARGE AMOUNT OF WATER. IF VOMITING OCCURS, KEEP AIRWAYS OPEN. KEEP HEAD LOWER THAN THE HIPS TO PREVENT ASPIRATION INTO THE LUNGS.

ALWAYS SEEK IMMEDIATE MEDICAL ATTENTION

FOR MEDICAL EMERGENCIES CALL 1-800-424-9300

RECOMMENDED PROCEDURES FOR TEAT SANITATION

A. PRE-MILKING (PRE-DIPPING)

1. Remove visible soils from the teats.

2. Observe foremilk by stripping two or three streams of milk into a strip cup.

3. Dip or spray the cow's teats full length with GENESIS 110 TEAT DIP.

4. Wait approximately 30 seconds.

5. Remove all teat dip by thoroughly drying the teats and teat orifices with a clean, single service paper towel(s).

6. Attach milking unit.

B.POST-MILKING (POST-DIPPING)

Immediately after milking, dip or spray all teats full length with GENESIS 110 TEAT DIP. Ensure good coverage of all sides of the teats and teat orifices.

GENERAL RECOMMENDATIONS

1. Use teat dip applicators made of plastic or other non-corrosive materials.Do not use cups made of aluminum.

2. When solution in the teat dip cup becomes dirty and/or noticeably loses color, discard remaining contents and refill up with fresh teat dip.

3. Do not use this product for cleaning or sanitizing equipment.

4.Wash teat dip cups after each milking.